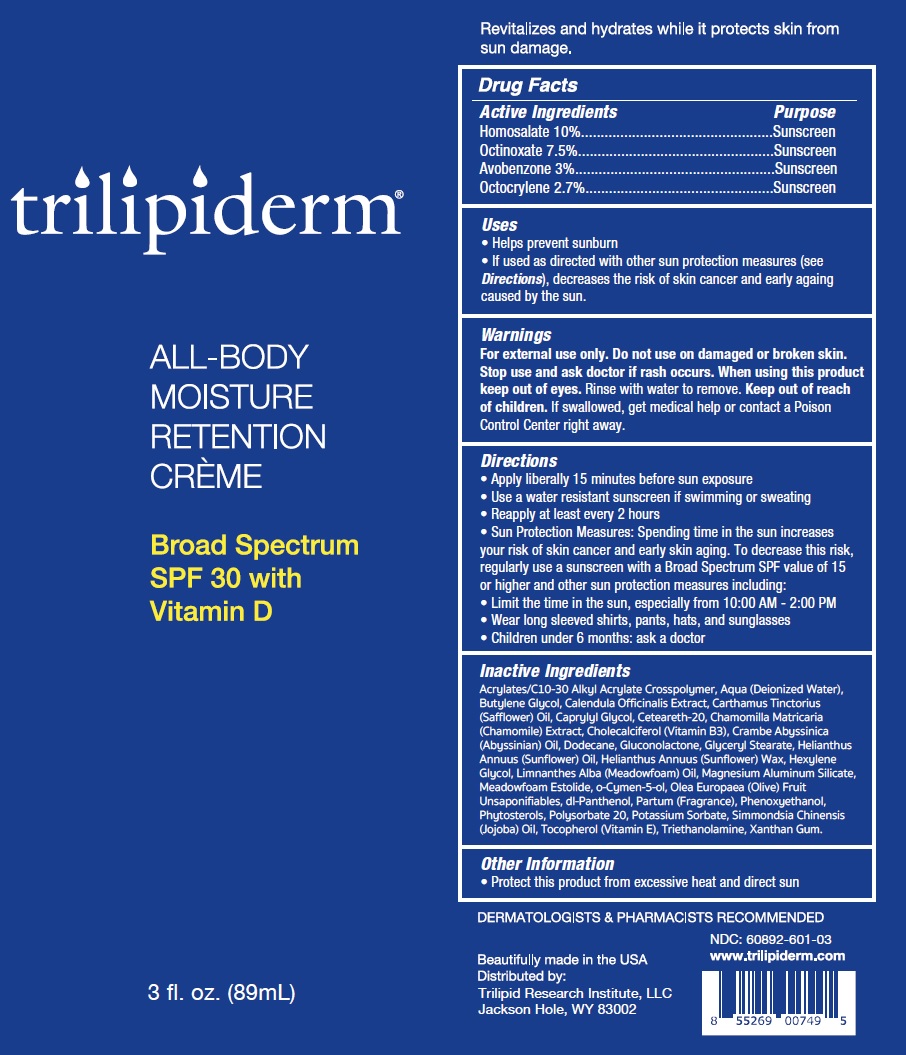 DRUG LABEL: TRILIPIDERM All-Body Moisture Retention Cream SPF-30
NDC: 60892-605 | Form: CREAM
Manufacturer: Trilipid Research Institute, LLC
Category: otc | Type: HUMAN OTC DRUG LABEL
Date: 20250403

ACTIVE INGREDIENTS: HOMOSALATE 100 mg/1 mL; OCTINOXATE 75 mg/1 mL; AVOBENZONE 30 mg/1 mL; OCTOCRYLENE 27 mg/1 mL
INACTIVE INGREDIENTS: WATER; BUTYLENE GLYCOL; CALENDULA OFFICINALIS FLOWER; SAFFLOWER; CAPRYLYL GLYCOL; POLYOXYL 20 CETOSTEARYL ETHER; CHAMOMILE; CHOLECALCIFEROL; DODECANE; GLUCONOLACTONE; GLYCERYL MONOSTEARATE; HELIANTHUS ANNUUS FLOWERING TOP; HEXYLENE GLYCOL; MAGNESIUM ALUMINUM SILICATE; MEADOWFOAM ESTOLIDE; O-CYMEN-5-OL; GREEN OLIVE; PANTHENOL; PHENOXYETHANOL; POLYSORBATE 20; POTASSIUM SORBATE; JOJOBA OIL; TOCOPHEROL; TROLAMINE; XANTHAN GUM

TRILIPIDERM All-Body Moisture Retention Cream SPF-30

Active Ingredients

Homosalate 10% Octinoxate 7.5% Avobenzone 3% Octocrylene 2.7%

Purpose

Sunscreen

Uses

• Helps prevent sunburn

• If used as directed with other sun protection measures (see Directions), decreases the risk of skin cancer and early againg caused by the sun.

Warnings

For external use only.

Do not use

on damaged or broken skin.

Stop use and ask doctor

if rash occurs.

When using this product

keep out of eyes. Rinse with water to remove.

Keep out of reach of children.

If swallowed, get medical help or contact a Poison Control Center right away.

Directions

• Apply liberally 15 minutes before sun exposure • Use a water resistant sunscreen if swimming or sweating • Reapply at least every 2 hours • Sun Protection Measures: Spending time in the sun increases your risk of skin cancer and early skin aging. To decrease this risk, regularly use a sunscreen with a Broad Spectrum SPF value of 15 or higher and other sun protection measures including: • Limit the time in the sun, especially from 10:00 AM - 2:00 PM • Wear long sleeved shirts, pants, hats, and sunglasses • Children under 6 months: ask a doctor

Inactive Ingredients

Acrylates/C10-30 Alkyl Acrylate Crosspolymer, Aqua (Deionized Water), Butylene Glycol, Calendula Officinalis Extract, Carthamus Tinctorius (Safflower) Oil, Caprylyl Glycol, Ceteareth-20, Chamomilla Matricaria (Chamomile) Extract, Cholecalciferol (Vitamin B3), Crambe Abyssinica (Abyssinian) Oil, Dodecane, Gluconolactone, Glyceryl Stearate, Helianthus Annuus (Sunflower) Oil, Helianthus Annuus (Sunflower) Wax, Hexylene Glycol, Limnanthes Alba (Meadowfoam) Oil, Magnesium Aluminum Silicate, Meadowfoam Estolide, o-Cymen-5-ol, Olea Europaea (Olive) Fruit Unsaponifiables, dl-Panthenol, Partum (Fragrance), Phenoxyethanol, Phytosterols, Polysorbate 20, Potassium Sorbate, Simmondsia Chinensis (Jojoba) Oil, Tocopherol (Vitamin E), Triethanolamine, Xanthan Gum.

Other Information

• Protect this product from excessive heat and direct sun